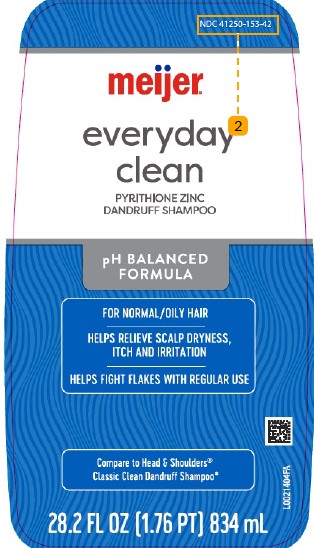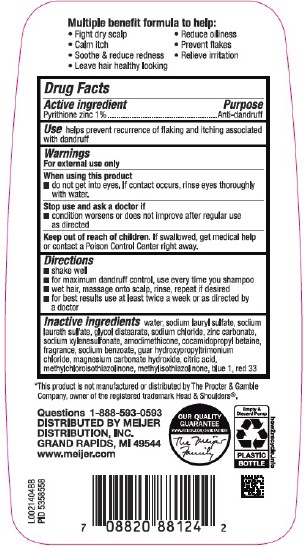 DRUG LABEL: Everyday Clean Dandruff
NDC: 41250-153 | Form: SHAMPOO
Manufacturer: Meijer, Inc.
Category: otc | Type: HUMAN OTC DRUG LABEL
Date: 20260219

ACTIVE INGREDIENTS: PYRITHIONE ZINC 10 mg/1 mL
INACTIVE INGREDIENTS: WATER; SODIUM LAURYL SULFATE; SODIUM LAURETH SULFATE; GLYCOL DISTEARATE; SODIUM CHLORIDE; ZINC CARBONATE; SODIUM XYLENESULFONATE; AMODIMETHICONE (800 CST); COCAMIDOPROPYL BETAINE; SODIUM BENZOATE; GUAR HYDROXYPROPYLTRIMONIUM CHLORIDE (1.7 SUBSTITUENTS PER SACCHARIDE); MAGNESIUM CARBONATE HYDROXIDE; CITRIC ACID MONOHYDRATE; METHYLCHLOROISOTHIAZOLINONE; METHYLISOTHIAZOLINONE; FD&C BLUE NO. 1; D&C RED NO. 33

Meijer 153.008/153BD
Everyday Clean Dandruff Shampoo

Claims

Multiple benefit formula to help:

- Fight dry scalp
- Calm itch
- Soothe & reduce redness
- Leave hair healthy looking
- Reduce oiliness
- Prevent flakes
- Relieve irritation

Active ingredient

Pyrithione zinc 1%

Purpose

Anti-Dandruff

Use

helps prevent recurrence of flaking and itching associated with dandruff

Warnings

For external use only

when using this product

- do not get into eyes. If contact occurs, rinse eyes thoroughly with water.

Stop use and ask a doctor if

- condition worsens or does not improve after regular use as directed

Keep out of reach of children.

If swallowed, get medical help or contact a Poison Control Center right away.

Directions

- shake well
- for maximum dandruff control, use every time you shampoo
- wet hair, massage onto scalp, rinse, repeat if desired
- for best results use at least twice a week or as directed by a doctor

Inactive ingredients

water, sodium lauryl sulfate, sodium laureth sulfate, glycol distearate, sodium chloride, zinc carbonate, sodium xylenesulfonate, amodimethicone, cocamidopropyl betaine, fragrance, sodium benzoate, guar hydroxypropyltrimonium chloride, magnesium carbonate hydroxide, citric acid, methylchloroisothiazolinone, methylisothiazolinone, blue 1, red 33

Disclaimer

*This product is not manufactured or distributed by The Procter & Gamble Company, owner of the registered trademark Head & Shoulders®.

Adverse reactions

Questions 1-888-593-0593

DISTRIBUTED BY MEIJER DISTRIBUTION, INC.

GRAND RAPIDS, MI 49544

www.meijer.com

OUR QUALITY GUARANTEE

WWW.MEIJER.COM/SATISFACTION

The MeijerFamily

Empty & Discard Pump

PLASTIC BOTTLE

how2recycle.info

principal display panel

NDC 41250-153-42

meijer®

everyday clean

PYRITHIONE ZINC

DANDRUFF SHAMPOO

pH BALANCED FORMULA

For Normal/Oily Hair

Helps relieve scalp dryness, itch and irritation

Helps fight flakes with regular use

Compare to Head & Shoulders®Classic Clean Dandruff Shampoo*

28.2 FL OZ (1.76 PT) 834 mL